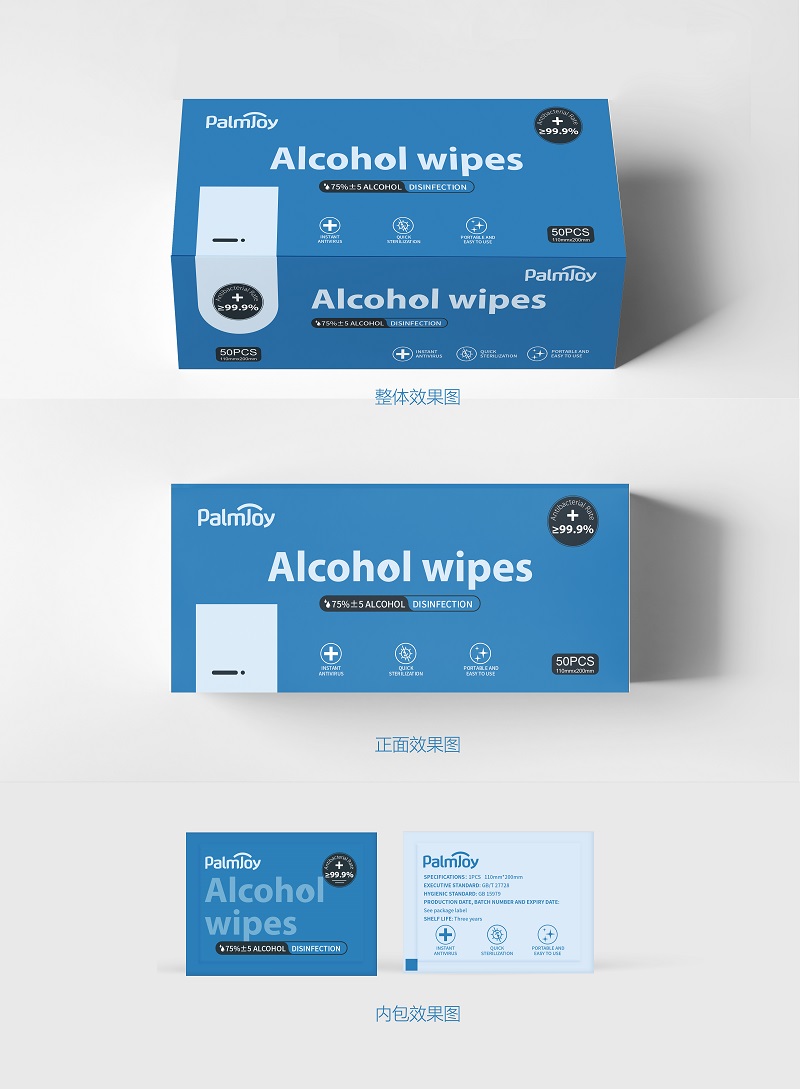 DRUG LABEL: Alcohol Wipes
NDC: 75543-101 | Form: PATCH
Manufacturer: Fujian Yifa Healthcare Products Co., Ltd.
Category: otc | Type: HUMAN OTC DRUG LABEL
Date: 20200505

ACTIVE INGREDIENTS: BENZALKONIUM CHLORIDE 0.15 U/100 U; DIDECYLDIMONIUM CHLORIDE 0.2 U/100 U; ALCOHOL 15 U/100 U
INACTIVE INGREDIENTS: GLYCERIN; PHENOXYETHANOL; WATER; PROPYLENE GLYCOL

Yifa, Alcohol Wipes, 3 AIs, *50

Active ingredient

Benzalkonium Chloride, 0.15% w/w;

Didecyldimonium Chloride, 0.2% w/w;

Ethanol Alcohol, 15% w/w.

Inactive ingredient

Phenoxyethanol, Propylene Glycol, Glycerin, Water.

Purpose

Sterilization.

When using

Skin’s cleaning care, Article surface’s cleaning and maintenance.

Do not use

- on children less than 2 months of age
- on open skin wounds

Stop use

Discontinue use if allergic reactions occur.

Keep out of reach of children

Indications & usage

Skin’s cleaning care, Article surface’s cleaning and maintenance.

Remove seal, pull out sheet and wipe skin or articles.

(For external use only)

Dosage & administration

Use it as needed, after following the usage instructions.

For external use only.

Warnings

This product is disposable and should not be reused.

Check whether the package is in good condition before use. If the package is found to be untidy, it is not suitable for use.